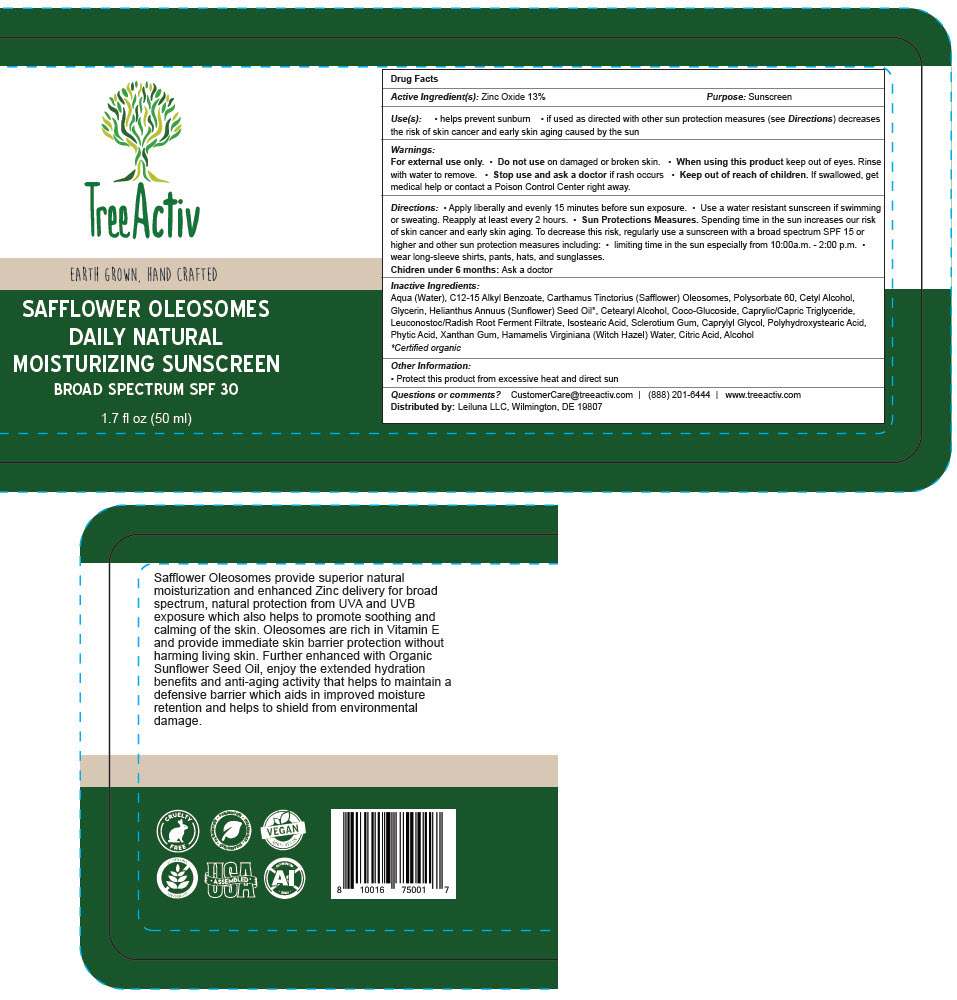 DRUG LABEL: TreeActiv Safflower Oleosomes Daily Natural Moisturizing Sunscreen Broad Spectrum SPF 30
NDC: 72841-101 | Form: LOTION
Manufacturer: Leiluna LLC
Category: otc | Type: HUMAN OTC DRUG LABEL
Date: 20190415

ACTIVE INGREDIENTS: ZINC OXIDE 130 mg/1 mL
INACTIVE INGREDIENTS: ALCOHOL; WATER; ALKYL (C12-15) BENZOATE; SAFFLOWER OIL; POLYSORBATE 60; CETYL ALCOHOL; GLYCERIN; SUNFLOWER OIL; CETOSTEARYL ALCOHOL; COCO GLUCOSIDE; ISOSTEARIC ACID; MEDIUM-CHAIN TRIGLYCERIDES; LEUCONOSTOC/RADISH ROOT FERMENT FILTRATE; BETASIZOFIRAN; WITCH HAZEL; XANTHAN GUM; CITRIC ACID ACETATE; POLYHYDROXYSTEARIC ACID (2300 MW); CAPRYLYL GLYCOL; FYTIC ACID

TreeActiv Safflower Oleosomes Daily Natural Moisturizing Sunscreen Broad Spectrum SPF 30

Drug Facts

Active Ingredient(s)

Zinc Oxide 13%

Purpose

Sunscreen

Use(s)

- helps prevent sunburn
- if used as directed with other sun protection measures (see Directions) decreases the risk of skin cancer and early skin aging caused by the sun

Warnings

For external use only.

- Do not use on damaged or broken skin.

- When using this product keep out of eyes. Rinse with water to remove.

- Stop use and ask a doctor if rash occurs

- Keep out of reach of children. If swallowed, get medical help or contact a Poison Control Center right away.

Directions

- Apply liberally and evenly 15 minutes before sun exposure.
- Use a water resistant sunscreen if swimming or sweating. Reapply at least every 2 hours.
- Sun Protections Measures. Spending time in the sun increases our risk of skin cancer and early skin aging. To decrease this risk, regularly use a sunscreen with a broad spectrum SPF 15 or higher and other sun protection measures including:
  - limiting time in the sun especially from 10:00a.m. - 2:00 p.m.
  - wear long-sleeve shirts, pants, hats, and sunglasses.

Chidren under 6 months: Ask a doctor

Inactive Ingredients

Aqua (Water), C12-15 Alkyl Benzoate, Carthamus Tinctorius (Safflower) Oleosomes, Polysorbate 60, Cetyl Alcohol, Glycerin, Helianthus Annuus (Sunflower) Seed Oil [Certified organic] , Cetearyl Alcohol, Coco-Glucoside, Caprylic/Capric Triglyceride, Leuconostoc/Radish Root Ferment Filtrate, Isostearic Acid, Sclerotium Gum, Caprylyl Glycol, Polyhydroxystearic Acid, Phytic Acid, Xanthan Gum, Hamamelis Virginiana (Witch Hazel) Water, Citric Acid, Alcohol

Other Information

- Protect this product from excessive heat and direct sun

Questions or comments?

CustomerCare@treeactiv.com | (888) 201-6444 | www.treeactiv.com

Distributed by: Leiluna LLC, Wilmington, DE 19807

PRINCIPAL DISPLAY PANEL - 50 ml Bottle Label

TreeActiv

EARTH GROWN, HAND CRAFTED

SAFFLOWER OLEOSOMES
DAILY NATURAL
MOISTURIZING SUNSCREEN

BROAD SPECTRUM SPF 30

1.7 fl oz (50 ml)